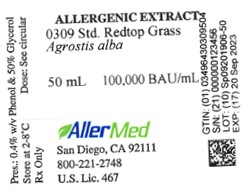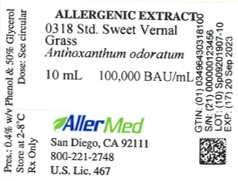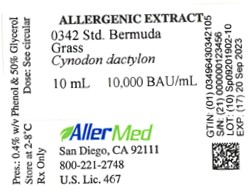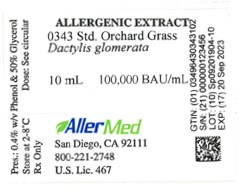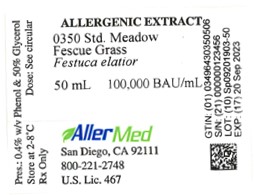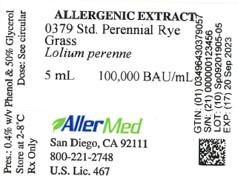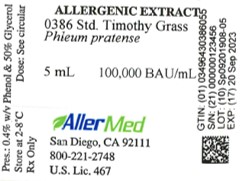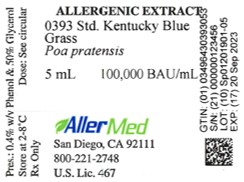 DRUG LABEL: Standardized Meadow Fescue Grass
NDC: 49643-350 | Form: INJECTION
Manufacturer: Allermed Laboratories, Inc.
Category: prescription | Type: HUMAN PRESCRIPTION DRUG LABEL
Date: 20250603

ACTIVE INGREDIENTS: LOLIUM PRATENSE POLLEN 100000 [BAU]/1 mL
INACTIVE INGREDIENTS: SODIUM BICARBONATE 0.00125 g/1 mL; PHENOL 0.004 g/1 mL; WATER; GLYCERIN 0.53 mL/1 mL; SODIUM CHLORIDE 0.0025 g/1 mL

ALLERGENIC EXTRACT Standardized Grass: Bermuda, Kentucky Blue (June), Meadow
Fescue, Orchard, Perennial Rye, Redtop, Sweet Vernal, Timothy

WARNINGS

This product is intended for use by physicians who are experienced in the administration of allergenic extract or for use under the guidance of an allergy specialist. In previously untreated patients, the initial dose must be based on skin testing as described in the dosage and administration section of this insert. Patients being switched from alum-adsorbed or other types of precipitated extracts to this extract should be started as though they were coming under treatment for the first time. Patients should be instructed to recognize adverse reaction symptoms and cautioned to contact the physician's office if symptoms occur. As with all allergenic extracts, severe systemic reactions may occur and in certain individuals these reactions may be lifethreatening or cause death. Patients should be observed for at least 20 minutes following treatment. Emergency measures as well as personnel trained in their use should be immediately available in the event of a life-threatening reaction. Patients being switched to a new lot of extract from the same manufacturer should have the dose reduced 75 percent. For dose selection in switching patients from unstandardized to standardized extract, physicians may refer to Table 3 as a guide (see CLINICAL PHARMACOLOGY). Extracts labeled in BAU/mL are not directly interchangeable with any other grass pollen product.

Patients receiving beta-blocking drugs may be refractive to the usual dose of epinephrine, in the event that epinephrine is required to control an adverse allergic reaction to this product. Caution must be exercised in testing and treating patients with steroid-dependent or labile asthma. This product should never be injected intravenously. See also WARNINGS and ADVERSE REACTIONS below.

Serious adverse reactions to this product should be reported to VAERS at 1-800-822-7967 or www.vaers.hhs.gov.

DESCRIPTION

Standardized grass pollen extract is a sterile solution containing the extractables of grass pollen in 0.25% sodium chloride, 0.125% sodium bicarbonate, 50% glycerol v/v and 0.4% phenol w/v. Standardized grass pollen extracts include Bermuda Grass (Cynodon dactylon), June Grass (Poa pratensis), Meadow Fescue Grass (Festuca elatior), Orchard Grass (Dactylis glomerata), Perennial Rye Grass (Lolium perenne), Redtop Grass (Agrostis alba), Sweet Vernal Grass (Anthoxanthum odoratum) and Timothy Grass (Phleum pratense).

The extract may be administered by the scratch, prick, puncture, or intradermal methods of skin testing for diagnostic purposes and subcutaneously for therapeutic purposes as directed under Dosage and Administration.

The potency of standardized grass pollen extracts is expressed in Bioequivalent Allergy Units per mL (BAU/mL) and is determined by an in vitro ELISA Competition Assay comparing the extract to a U.S. reference grass pollen extract available from the Center for Biologics Evaluation and Research (CBER), U.S. Food and Drug Administration. Bioequivalent Allergy Units per mL (BAU/mL) have been assigned to the reference extract based on quantitative skin testing (see CLINICAL PHARMACOLOGY). CBER reference extract labeled 100,000 BAU/mL can be diluted 1:5 million and yield a 50 mm sum of erythema diameter response intradermally in highly puncture reactive subjects. CBER reference extract labeled 10,000 BAU/mL can be diluted 1:500,000 for the same response (12).

Allermed's standardized grass pollen extracts labeled in BAU/mL are not interchangeable with alum-precipitated grass pollen extracts, grass pollen extracts labeled in AU/mL or non-standardized grass pollen extracts.

CLINICAL PHARMACOLOGY

It is estimated that grass pollen is responsible for 10 - 30% of all IgE-mediated allergies worldwide (1). Temperate grasses, including Dactylis glomerata (Orchard Grass), Lolium perenne (Rye Grass), Phleum pratense (Timothy Grass) and Poa pratensis (Blue Grass), have practically identical allergenic characteristics. Subtropical grasses, such as Cynodon dactylon (Bermuda Grass), are antigenically distinct from temperate grasses and should be regarded as separate allergenic sources. For effective testing and treatment with grass pollen extracts, the extracts must be properly selected to represent the allergenic enviornment of the allergic individual (1,2,3,4).

Grass pollen extract may have as many as 40 components, of which 5 - 10 may be allergenic. The most important allergens are classified into groups I - VI. Allergens in these groups account for 90 - 100% of the IgE binding prevalence in the serum of grass pollen allergenic patients (1,5).

The pharmacologic action of grass pollen extract used diagnostically is based on the liberation of histamine and other substances when allergens in the extract react with specific IgE antibody attached to mast cells. The release of pharmacologically active mediators from mast cell results in the wheal-flare reaction associated with a positive skin test (6,7).

The basis for the clinical improvement of allergic symptoms following immunotherapy with grass pollen extract is not clearly understood. Several immunologic changes have been demonstrated that might be responsible for the amelioration of allergenic symptoms. These changes include (a) increase in serum IgG antbodies, (b) blunting of the seasonal rise of IgE antibodies, (c) elevation of blocking IgA/IgG antibodies in secretions, (d) reduced basophil reactivity and sensitivity to allergens and (e) reduced in vitro lymphocyte responsiveness to allergens (8). There is evidence that symptoms are effectively altered only by the administration of the relevant allergen (9,10,11).

The results shown in Table 1 were observed with 10,000 BAU/mL reference extract administered to 15 highly sensitive grass allergic persons by the puncture method (data on file at FDA). The intradermal doses (BAU/mL) of grass pollen extracts required to elicit 50 mm sum of erythema are shown in Table 2 (12).

Table 1. Puncture data (bifurcated needle) with 10,000 BAU/mL reference grass pollen extracts.
 |  |  | P∑E (mm) [P∑E = Sum of erythema of the longest and orthogonal diameters.] |  | P∑W (mm) [P∑W = Sum of edema (wheal) of the longest and orthogonal diameters.]
Reference Pollen | FDA lot | N | Mean | Range | Mean | Range
Bermuda | E4-Ber | 15 | 90.3 | 43 - 123 | 15.7 | 7 - 31
June | E3-Jkb | 15 | 77.3 | 47 - 107 | 15.9 | 6 - 28
Meadow Fescue | E4-MF | 15 | 81.1 | 57 - 115 | 11.9 | 7 - 22
Orchard | E4-Or | 15 | 84.3 | 57 - 111 | 14.1 | 9 - 19
Perennial Rye | E10-Rye | 15 | 92.3 | 73 - 135 | 17.5 | 6 - 36
Redtop | E4-RE | 15 | 77.1 | 42 - 98 | 14.1 | 8 - 19
Sweet Vernal | E4-SV | 15 | 81.2 | 28 - 123 | 15.7 | 8 - 30
Timothy | E6-Ti | 15 | 88.3 | 51- 109 | 16.9 | 8 - 40

Note: Relative potency compared to the U.S. Reference with potency of 1.0. the U.S. Reference for Bermuda Grass is 10,000 BAU/mL (range: 6,900 - 143,000 BAU/mL). The U.S References for other grasses are 100,000 BAU/mL (range: 69,000 - 143,000 BAU/mL).

INDICATIONS AND USAGE

Standardized grass pollen extract is indicated for use in the diagnosis of grass allergy in patients with a history of allergic symptoms that occur during grass pollination. Skin tests with standardized grass pollen extract should be done first by the puncture method using 10,000 BAU/mL extract. If these tests are negative, they may be repeated by the puncture method with 100,000 BAU/mL extract, or by the intradermal method using an appropriate dilution (see DOSAGE AND ADMINISTRATION). The extract also is indicated for use in the treatment of allergic symptoms by immunotherapy in patients with a history of grass pollen allergy and established sensitivity to grass pollen extract by skin testing. The availability of 10,000 and 100,000 BAU/mL extracts facilitates dose selection for safe switching to standardized grass pollen extracts. Previously untreated patients should be initially treated with appropriately diluted 10,000 BAU/mL. If tolerated, higher doses may be indicated.

The use of grass pollen extract for the above purposes should be made only by physicians with special familiarity and knowledge of allergy as described in a standard allergy textbook (13).

Allermed's standardized grass pollen extracts labeled in BAU/mL are not interchangeable with alum-precipitated grass pollen extracts, grass pollen extracts labeled in AU/mL or non-standardized grass pollen extracts.

CONTRAINDICATIONS

Immunotherapy should not be started in patients until a specific diagnosis of Type I allergy to grass pollen has been made from the patient's allergy history and from a positive skin test to grass pollen extract. Other contraindications include:

EXTREME SENSITIVITY TO GRASS POLLEN: Patients who experience serious adverse reactions to grass pollen extract from skin testing and/or immunotherapy should not be given the product.

AUTOIMMUNE DISEASE: Individuals with autoimmune disease may be at risk, due to the possibility of routine immunizations exacerbating symptoms of the underlying disease.

MYOCARDIAL INFARCTION: Patients who have experienced a recent myocardial infarction may not be able to tolerate adverse reactions resulting from skin testing or immunotherapy. The benefit-torisk ratio must be carefully evaluated in these patients.

CHILDREN WITH NEPHROTIC SYNDROME: Children with nephrotic syndrome require careful consideration and probably should not receive immunotherapy, due to a variety of seemingly unrelated events that may cause an exacerbation of nephrotic disease.

BLEEDING DIATHESIS: Injections of grass pollen extract should not be administered in the presence of diseases characterized by a bleeding diathesis.

WARNINGS

Standardized grass pollen extract must be diluted prior to first use on a patient for immunotherapy or intradermal testing (see DOSAGE AND ADMINISTRATION). Grass pollen extract is manufactured to assure high potency and has the ability to cause serious local and systemic reactions, including death in sensitive patients (14). Patients should be informed of this risk and precautions should be discussed prior to initiating skin testing and immunotherapy (see PRECAUTIONS).

Grass pollen extract should be temporarily withheld from a patient if any of the following conditions exist: (a) severe symptoms of rhinitis and/or asthma; (b) infection or flu accompanied by fever; (c) exposure to excessive amounts of grass pollen allergen prior to a scheduled injection.

SWITCHING PATIENTS TO STANDARDIZED GRASS POLLEN EXTRACT: The same precautions that are recommended in switching from an old to a new lot of non-standardized grass pollen extract should be followed in switching from non-standardized to standardized grass pollen extract, i.e., the dose of the new lot of standardized grass pollen extract should be reduced 75% of the dose given from an old lot of non-standardized grass pollen extract. Under certain circumstances, it may be advisable to compare the relative potency of the standardized and non-standardized extract by side by side skin testing using comparable v/v dilutions of the concentrates.

When switching from alum precipitated grass pollen extract to standardized grass pollen extract, the patient should be managed as a new patient coming under treatment for the first time.

PRECAUTIONS

GENERAL: The risk of a severe allergic reaction usually can be reduced by eliciting the patient's allergy history and by percutaneous testing by the scratch, prick or puncture method. If a scratch, prick or puncture skin test is negative, it usually is safe to perform an intradermal test with a one thousand-fold dilution of the extract used for the percutaneous test. If there is a history of unusual sensitivity, it is advisable to use a weaker dilution of the extract for skin testing.

Systemic allergic reactions may occur as a result of immunotherapy. The risk can be reduced by adherence to a careful injection schedule, which starts with a low concentration of extract and is increased slowly. The physician must be prepared to treat anaphylaxis should it occur and have the necessary drugs and equipment on hand to treat serious adverse reactions. Extracts should not be administered by the patient or by other individuals who are not prepared to treat anaphylaxis, should it occur.

Extract must be injected subcutaneously during immunotherapy. It must not be given intravenously. A separate sterile tuberculin syringe graduated in 0.01 mL should be used for each injection.

INFORMATION FOR PATIENTS: Because most serious reactions occur within 20 minutes after the injection of allergenic extract the patient should remain under observation for this length of time. The patient also should be instructed to report any unusual reactions to the physician, such as swelling and/or tenderness at the injection site or rhinorrhea, sneezing, coughing, wheezing, shortness of breath, nausea, dizziness or faintness following the injection of extract.

CARCINOGENESIS, MUTAGENESIS, IMPAIRMENT OF FERTILITY: Long term studies in animals have not been conducted with standardized grass pollen extract to determine the potential for carcinogenicity, mutagenicity or impairment of fertility.

PREGNANCY CATEGORY C: Animal reproduction studies have not been conducted with standardized grass pollen extract. It is also not known whether standardized grass pollen extract can cause fetal harm when administered to a pregnant woman or can affect reproduction capacity. Caution should be exercised in testing or treating pregnant females, because a systemic reaction might conceivably cause uterine muscle contractions leading to abortion. Standardized grass pollen extract should be given to a pregnant woman only if clearly needed (15).

PEDIATRIC USE: The dose of allergenic extract recommended for children is the same as for adults. Allowances may be made in the injection of large doses of extract for treatment. In this case, it may be advisable to modify the dose and frequency of injections, so that the discomfort is minimized.

NURSING MOTHERS: It is not known whether standardized grass pollen extract is excreted in human milk. Because many drugs are excreted in human milk, caution should be exercised when allergenic extract is administered to a nursing woman.

DRUG INTERACTION: Antihistamines and hydroxyzine can inhibit the immediate skin test reaction. Patients being treated with delayed absorption antihistamine tablets should be free of such medication for 48 hours before testing. Non-sedating antihistamines, such as terfenadine and astemizole, may variably suppress the skin response for longer periods of time up to six weeks. Epinephrine injection inhibits the immediate skin test reaction for several hours. Beta-blocking drugs may make a patient refractory to the usual dose of epinephrine, in the event epinephrine is required to treat an adverse allergic reaction.

ADVERSE REACTIONS

Local reactions consisting of erythema, itching, swelling, tenderness and sometimes pain may occur at the injection site. These reactions may appear within a few minutes to hours and persist for several days. Local cold applications and oral antihistamines may be effective treatment. For marked and prolonged local reactions, steroids may be helpful.

Adverse systemic reactions usually occur within minutes and consist primarily of allergic symptoms such as generalized skin erythema, urticaria, pruritus, angioedema, rhinitis, wheezing, laryngeal edema and hypotension. Less commonly, nausea, emesis, abdominal cramps, diarrhea and uterine contractions may occur. Severe reactions may cause shock and loss of consciousness and fatalities have occurred (14).

The treatment of systemic allergic reactions is somewhat dependent upon the symptom complex. Epinephrine hydrochloride 1:1,000 aqueous, in an adult dose of 0.3 - 0.5 mL (or 0.01 mL per kg. for children) administered subcutaneously in the opposite arm is the immediate treatment of choice. A tourniquet should be placed above the site of the injection if the injection was done on the extremities. Antihistamines may offer relief of recurrent urticaria, associated skin reactions and gastrointestinal symptoms. Persistent wheezing may necessitate intravenous aminophylline treatment in addition to inhaled bronchodilators. For profound shock and hypotension, intravenous fluids, vasopressors and oxygen also may be needed. Maintenance of an open airway is critical if upper airway obstruction is present. Corticosteroids may provide benefit if symptoms are prolonged or recurrent.

Serious adverse reactions to this product should be reported to MEDWATCH, Food and Drug Administration, 5600 Fishers Lane, Rockville, MD 20852-9782. Telephone (800) 332-1088.

OVERDOSAGE

A strong local reaction to the injection of extract may be treated with oral antihistamines and the local application of a cold compress. The dosage must be reduced and additional extract must not be given until all evidence of the reaction has disappeared. A systemic reaction following the injection of extract must be treated immediately with Epinephrine hydrochloride 1:1,000 aqueous and other measures as appropriate (see ADVERSE REACTIONS, paragraph 3 above).

DOSAGE AND ADMINISTRATION

Parental drug products should be inspected visually for particulate matter and discoloration prior to adminitration, whenever solution and container permit. The product should be discarded if discoloration or particles are observed.

DIAGNOSTIC USE: Standardized grass pollen extract may be used to diagnose sensitivity to grass pollen by performing skin tests on persons with a history of grass pollen allergy. Due to the risk of adverse reactions occuting in highly sensitive persons, it is mandatory to initially test all patients percutaneously using the scratch, prick or puncture method. If a properly performed percutaneous test is negative, an intradermal test may be used with caution.

PUNCTURE TEST: The punture test should be performed first with 10,000 BAU/mL extract. Data for the puncture test using 10,000 BAU/mL extract are summarized in Table 1 under CLINICAL PHARMOCOLOGY. If the puncture test to 10,000 BAU/mL extract is negative, the test may be repeated using 100,000 BAU/mL extract. Appropriate positive and negative controls for skin test interpretation are necessary. Reactions are quarntified based on size of erythema and wheal in reaction to controls.

INTRADERMAL TEST: An intradermal test should only be performed after a puncture test has been properly administered with a negative result. It is usually safe to initiate intradermal testing with a 1:1,000 v/v diluton of the extract to which a negative puncture test was observed. For example, if a puncture test is done with 10,000 BAU/mL extract and is negative, the intradermal test may be performed with 0.05 mL of 10 BAU/mL extract. The dose may be increased to 0.05 mL of 100 BAU/mL extract if the intradermal test with 10 BAU/mL extract is negative.

THERAPEUTIC USE: The dosage of grass pollen extract administered by subcutaneous injection during immunotherapy is highly individualized and varies according to the patient. In patients who appear to be highly sensitive by history and skin test, the initial dose of the extract should be low, such as 0.1 mL of a 0.01 BAU/mL dilution. The amount of extract is increased at each injection, but not more than 50%-100% of the previous amount, and the next increment is governed by the response to the last injection. Local reactions that persist longer than 24 hours are undesirable and any systemic reaction is an indication that the dose should be reduced (at least 50%). The upper limits of dosage have not been established, but doses larger than 0.2 mL of concentrate containing 50% glycerol may be painful due to the glycerol in the extract. The potency of each standardized grass pollen in a final mixture should not exceed that obtained from using a 10,000 BAU/mL stock concentrate of each grass included in the mix. Concentrate containing 100,000 BAU/mL should be diluted to 10,000 BAU/mL extract before being used to prepare final mixtures, or alternatively, the volume of 100,000 BAU/mL extract added to the mixture should be reduced 10-fold.

The optimum interval between doses of grass pollen extract has not been definitely established. However, as is customarily practiced, injections are given one or two times per week until the maintenance dose is reached. At this time, the injection interval may be increased to 2 weeks, then to 3 weeks and finally 4 weeks. If the patient does not return for 6 to 8 weeks after the last injection, the dose should be reduced to 50% of the last dose. If longer than 8 weeks, a dose reduction of one, two or three dilutions may be made, depending on the amount of time that has elapsed since the last injection. The dosage and the interval between injections may need to be modified according to the clinical response of the patient. When switching patients to fresh extract, the initial dose should be reduced 75% [one-quarter (25%) of the previous dose administered from the old lot of extract].

A period of three to five years of injection therapy constitutes an average course of treatment.

Children and geriatric patients appear to tolerate injections of allergenic extract well, and no special recommendations need to be made for these groups (see PRECAUTIONS - PEDIATRIC USE).

PREPARING DILUTIONS: To prepare dilutions for intradermal skin tests and therapeutic use, the stock concentrate may be diluted as shown in Table 4. Vial #1 is made by adding 1.0 mL of the concentrate to 9.0 mL of sterile diluent. This process is repeated until the desired concentration is achieved. Each new dilution is made by adding 1.0 mL of the previous dilution to 9.0 mL of sterile diluent. The number of allergy units per mL in each dilution is shown in Table 4.

Table 4. Directions for diluting standardized grass pollen extract containing 10,000 BAU/mL*
Extract | mL Extract | mL Diluent | Dilution Strength | Dilution Label
10,000 BAU/mL | 1.0 | 9.0 | 1,000 BAU/mL | A
Dilution A | 1.0 | 9.0 | 100 BAU/mL | B
Dilution B | 1.0 | 9.0 | 10 BAU/mL | C
Dilution C | 1.0 | 9.0 | 1.0 BAU/mL | D
Dilution D | 1.0 | 9.0 | 0.1 BAU/mL | E
Dilution E | 1.0 | 9.0 | 0.01 BAU/mL | F

*If 100,000 BAU/mL extract is used to prepare dilutions, the 100,000 BAU/mL extract should be diluted 1:10 v/v before the directions shown in the table are followed.

HOW SUPPLIED

Standardized grass pollen extract containing 10,000 BAU/mL is supplied in 1 and 5 mL dropper vials and in 10 mL, 30 mL and 50 mL multidose vials. Bermuda Grass is only supplied as 10,000 BAU/mL. Other standardized grass pollen extracts are available at 100,000 BAU/mL in 10 mL, 30 mL and 50 mL vials.

STORAGE AND HANDLING

The expiration date of standardized grass pollen extract is listed on the container label. The extract should be stored at 2 - 8°C, if possible, and kept in this temperature range during office use. Dilutions of the stock concentrate containing less than 50% glycerol are less stable. If loss of potency is suspected, such dilutions should be checked by skin testing with equal units of a freshly prepared dilution.

REFERENCES

1. Bierman, C.W., Pearlman, D.S., Shapiro, G.G., Busse, W.W. Allergy, asthma and immunology from infancy to adulthood, Third Edition, p. 533, W.B. Saunders, Philadelphia, 1996.
2. Martin, B.G., Mansfield, L.E., Nelson, H.S. Cross-allergenicity among the grasses, Ann. Allergy, 54: 99-104, 1985.
3. Milner, F.H., Tees, E.C. Specific sensitivity to individual grass pollens in some hay fever patients, Clinical Allergy. 2:83, 1972.
4. Frankland, A.W., Augustine, R. Grass pollen antigens effective in treatment, Clinical Science, 23:95, 1962.
5. Matthiesen, F., Lowenstein, H. Group V allergens in grass pollens. II. Investigation of group V allergens in pollens from 10 grasses. Clin. Exp. Allergy, 21:309-320, 1991.
6. Ting, S., Dunsky, E.H., Lavker, R.M., et al. Patterns of mast cell alterations and in vivo mediator release in human allergic skin reactions, J. Allergy Clin. Immunol, 66:417, 1980.
7. Zweiman, B. Mediators of allergic inflammation in the skin. Clin. Allergy, 18:419, 1988.
8. Creticos, P.S. Immunologic changes associated with immunotherapy, Immunol. Allergy Clin., North Am., 12:13-37, 1992.
9. Lowell, F.C., Franklin, W. A double-blind study of the effectiveness and specificity of injectiontherapy in ragweed hayfever. N. England J. Med., 273:675-679, 1965.
10. Norman, P.S., Lichtenstein, L.M. The clinical and immunologic specificity of immunotherapy, J. Allergy Clin. Immunol., 61:370-377, 1978.
11. Reid, M.J., Moss, R.B., Yoa-Pi, H., et al. Seasonal asthma in northern California: Allergic causes and efficacy of immunotherapy, J. Allergy Clin. Immunol., 78:590-600, 1986.
12. Turkeltaub, P.C. The allergy unit-clinical relevance: issues in allergen standardization. In: Lockey, R.F., S.C. Bukantz eds., Allergen Immunotherapy, Marcel Dekkar, New York, 171-190, 1991.
13. Middleton, E. Jr., Reed, C.E., Ellis, F.E., et al. Allergy Principles and practice, Fourth Edition, Vol. I, 573-594, Vol. II 1489-1509, Mosby, St. Louis, 1993.
14. Reid, M.J., Lockey, R.F., Turkeltaub, P.C., Platts-Mills, T.A.E. Survey of fatalities from skin testing and immunotherapy, J. Allergy Clin. Immunol., 92: 6-15, 1993.
15. Metzger, W.J., Turner, E., Patterson, R. The safety of immunotherapy during pregnancy, J. Allergy Clin. Immunol., 61:268, 1978.